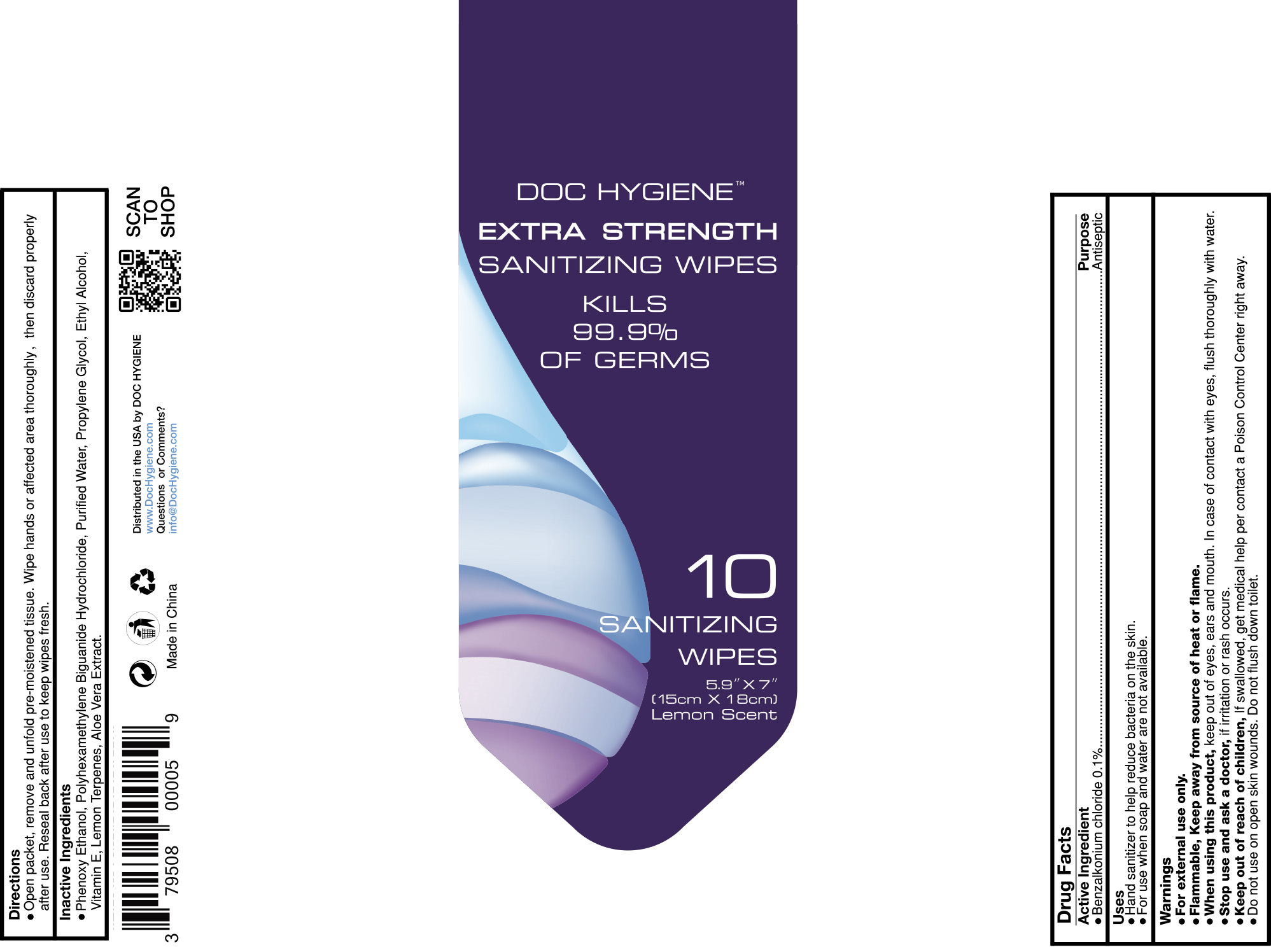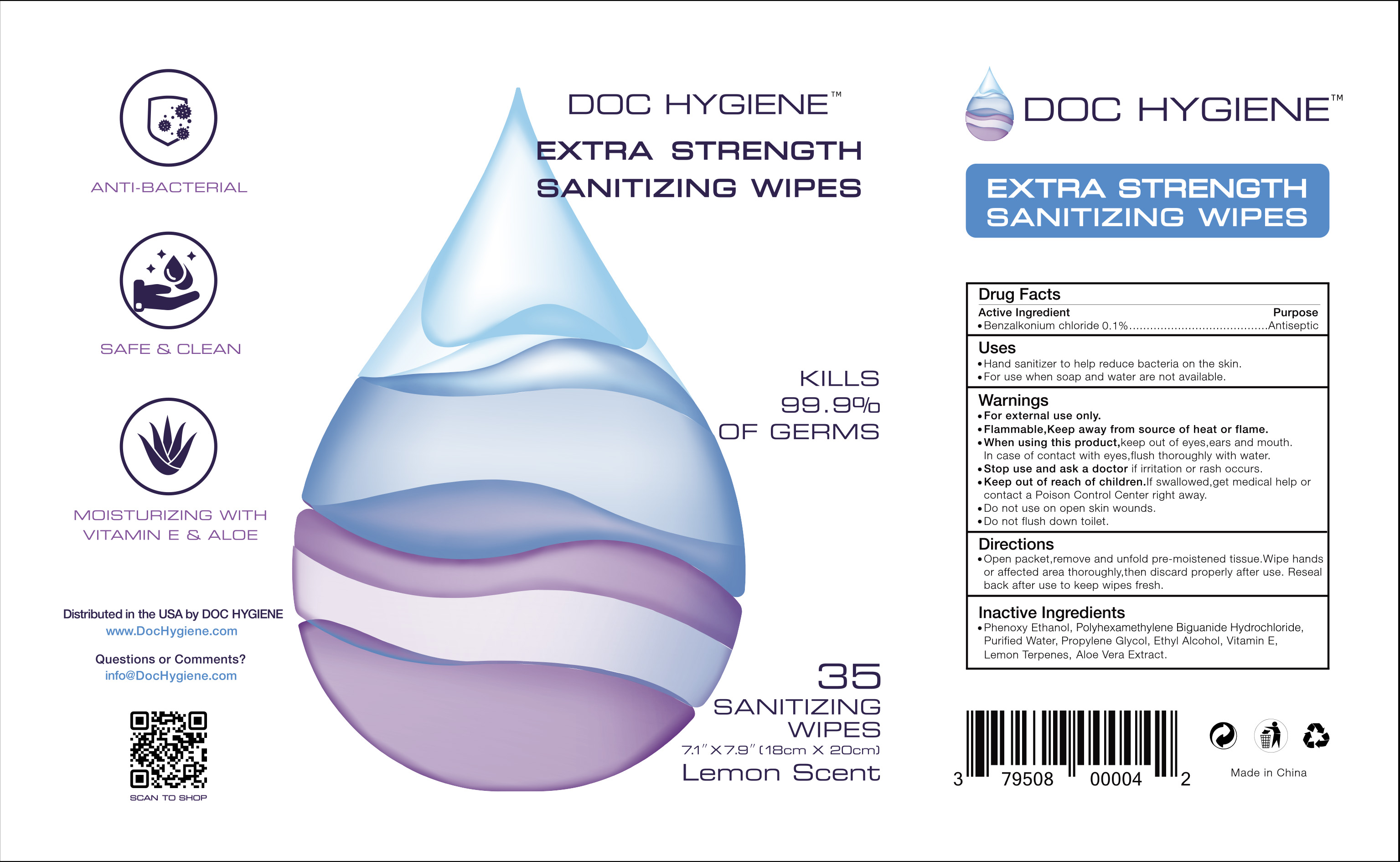 DRUG LABEL: Sanitizing Wipes
NDC: 80144-001 | Form: CLOTH
Manufacturer: Condor Co., Ltd.
Category: otc | Type: HUMAN OTC DRUG LABEL
Date: 20200825

ACTIVE INGREDIENTS: BENZALKONIUM CHLORIDE 0.1 mg/100 mg
INACTIVE INGREDIENTS: WATER 95.61 mg/100 mg; ALOE VERA LEAF 0.05 mg/100 mg; ALPHA-TOCOPHEROL 0.05 mg/100 mg; POLIHEXANIDE HYDROCHLORIDE 0.02 mg/100 mg; ALCOHOL 4 mg/100 mg; PROPYLENE GLYCOL 0.05 mg/100 mg; LEMON TERPENES 0.02 mg/100 mg; PHENOXYETHANOL 0.1 mg/100 mg

Sanitizing Wipes

ACTIVE INGREDIENT

Benzalkonium chloride 0.1%

PURPOSE

Antiseptic, Hand Sanitizer

PURPOSE

Antiseptic, Hand Sanitizer

INDICATIONS AND USAGE

Hand sanitizer to help reduce bacteria on the skin.

For use when soap and water are not available.

WARNINGS

For external use only. Flammable. Keep away from heat or flame

DO NOT USE

in children less than 2 months of age
on open skin wounds

When using this product keep out of eyes, ears, and mouth. In case of contact with eyes, rinse eyes thoroughly with water.
Stop use and ask a doctor if irritation or rash occurs. These may be signs of a serious condition.
Keep out of reach of children. If swallowed, get medical help or contact a Poison Control Center right away.

Stop use and ask a doctor if irritation or rash occurs. These may be signs of a serious condition.

Keep out of reach of children. If swallowed, get medical help or contact a Poison Control Center right away.

DOSAGE AND ADMINISTRATION

Open packet, remove and unfold pre-moistened tissue. Wipe hands or affected area thoroughly, then discard properly after use. Reseal back after use to keep wipes fresh.

STORAGE AND HANDLING

Store between 15-30C (59-86F)
Avoid freezing and excessive heat above 40C (104F)

INACTIVE INGREDIENT

Phenoxy Ethanol, Polyhexamethylene Biguanide Hydrochloride, Purified Water, Propylene Glycol, Ethyl Alcohol, Vitamin E, Lemon Terpenes, Aloe Vera Extract.

PACKAGE LABEL

10 wipes NDC: 80144-001-01

35 wipes NDC: 80144-001-02